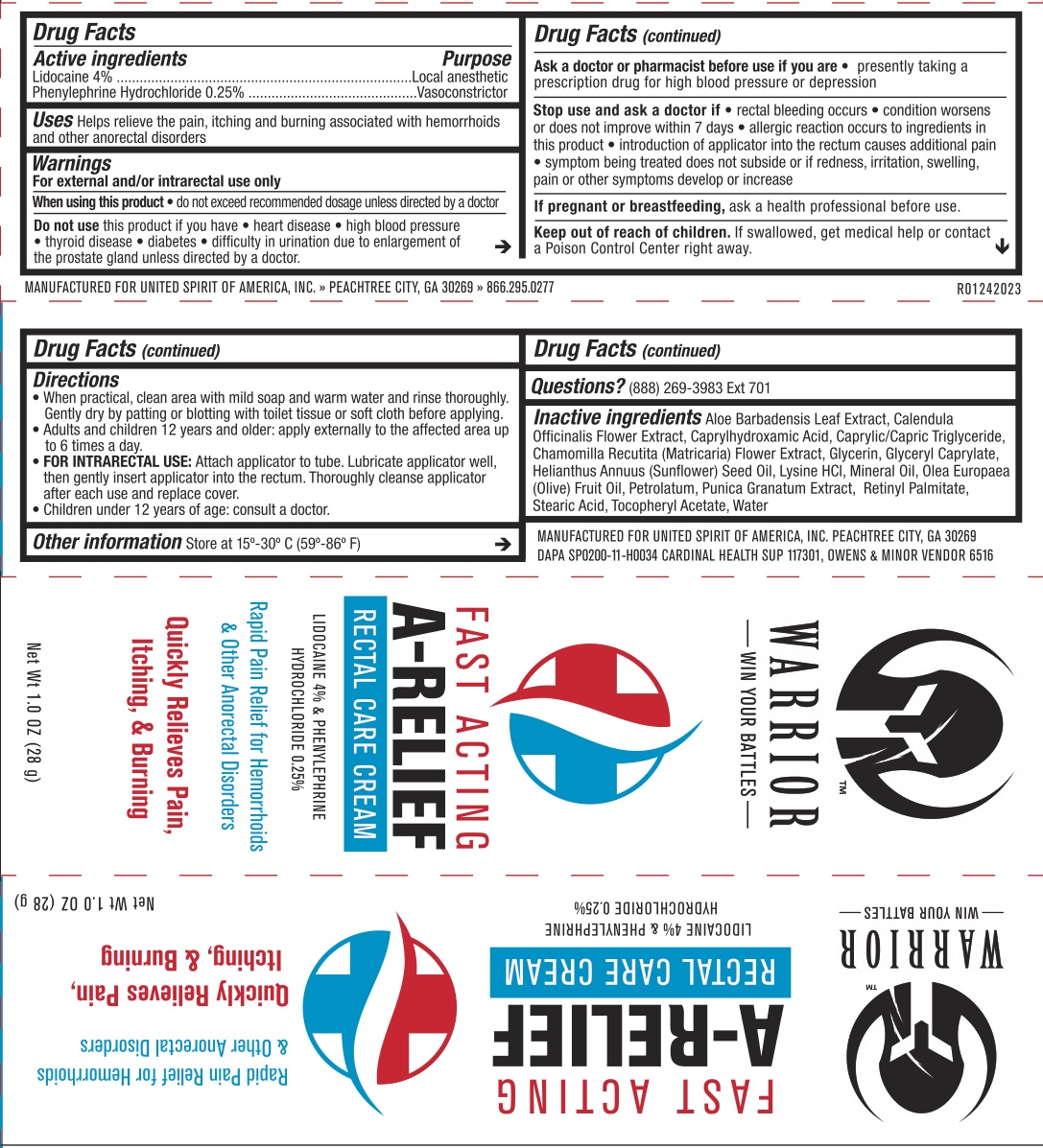 DRUG LABEL: Warrior Rectal Care
NDC: 72839-071 | Form: OINTMENT
Manufacturer: Derma Care Research Labs
Category: otc | Type: HUMAN OTC DRUG LABEL
Date: 20241215

ACTIVE INGREDIENTS: PHENYLEPHRINE HYDROCHLORIDE 0.25 g/100 g; LIDOCAINE 4 g/100 g
INACTIVE INGREDIENTS: SUNFLOWER OIL; GLYCERYL CAPRYLATE; GLYCERIN; ALOE; CALENDULA OFFICINALIS FLOWER; MEDIUM-CHAIN TRIGLYCERIDES; MATRICARIA CHAMOMILLA LEAF; CAPRYLHYDROXAMIC ACID; LYSINE HYDROCHLORIDE; MINERAL OIL; OLIVE OIL; PETROLATUM; PUNICA GRANATUM ROOT BARK; VITAMIN A PALMITATE; STEARIC ACID; .ALPHA.-TOCOPHEROL ACETATE; WATER

Warrior Rectal Care

ACTIVE INGREDIENT

Lidocaine 4%, Phenylephrine HCl 0.25%

PURPOSE

Analgesic (pain relief), Vasoconstrictor

INDICATIONS AND USAGE

Helps relieve the pain, itching, and burning associated with hemorrhoids and other anorectal disorders.

WARNINGS

For external and/or intrarectal use only.

When using this product do not exceed recommended daily dosage unless directed by a doctor.

Do not use this product if you have difficulty in urination due to enlargement of the prostate gland. Diabetes, heart disease, high blood pressure, thyroid disease. Presently taking a prescription for high blood pressure or depression.

Stop use and ask a doctor if condition worsens or does not improve within seven days, bleeding occurs. Introduction of applicator into the rectum causes additional pain.

KEEP OUT OF REACH OF CHILDREN

If swallowed, seek medical help or contact a Poison Control Center right away.

DOSAGE AND ADMINISTRATION

Children under 12 years of age consult your pediatrician.

Adults: apply to affected area up to 4 times daily.

Clean affected area with mild soap and warm water, rinse thoroughly, and then gently dry (patting or blotting) with tissue or soft cloth before use.

FOR INTRARECTAL USE: attach applicator to tube. Lubricate applicator well, then gently insert applicator into the rectum. Thoroughly cleanse applicator after each use and replace cover.

INACTIVE INGREDIENT

Aloe Barbadensis Leaf Extract, Calendula Officinalis Flower Extract, Caprylhydroxamic Acid, Caprylic/Capric Triglyceride, Chamomilla Recutita (Matricaria) Flower Extract, Glycerin, Glyceryl Caprylate, Helianthus Annuus (Sunflower) Seed Oil, Lysine HCl, Mineral Oil,
Olea Europaea (Olive) Fruit Oil, Petrolatum, Punica Granatum Extract, Retinyl Palmitate, Stearic Acid, Tocopheryl Acetate, Water

PREGNANCY OR BREAST FEEDING

Ask a health professional before use.